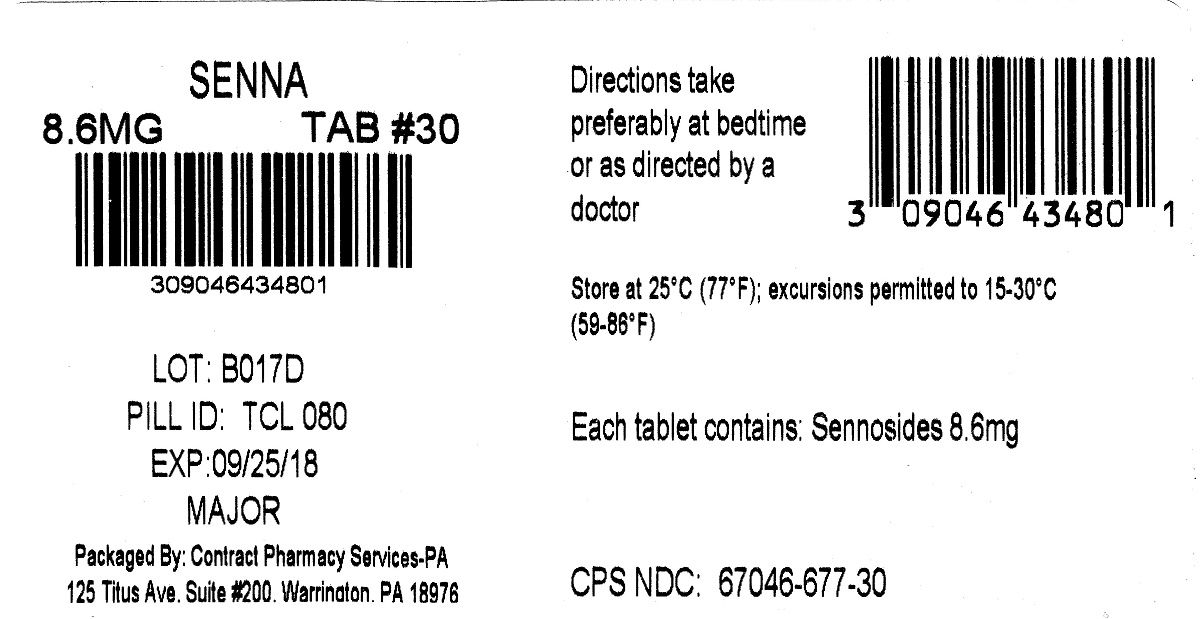 DRUG LABEL: SENNA
NDC: 67046-677 | Form: TABLET, COATED
Manufacturer: Contract Pharmacy Services-PA
Category: otc | Type: HUMAN OTC DRUG LABEL
Date: 20170925

ACTIVE INGREDIENTS: SENNOSIDES A AND B 8.6 mg/1 1
INACTIVE INGREDIENTS: CROSCARMELLOSE SODIUM; DIBASIC CALCIUM PHOSPHATE DIHYDRATE; HYPROMELLOSES; MAGNESIUM STEARATE; CELLULOSE, MICROCRYSTALLINE; MINERAL OIL

677 Senna 8.6 mg